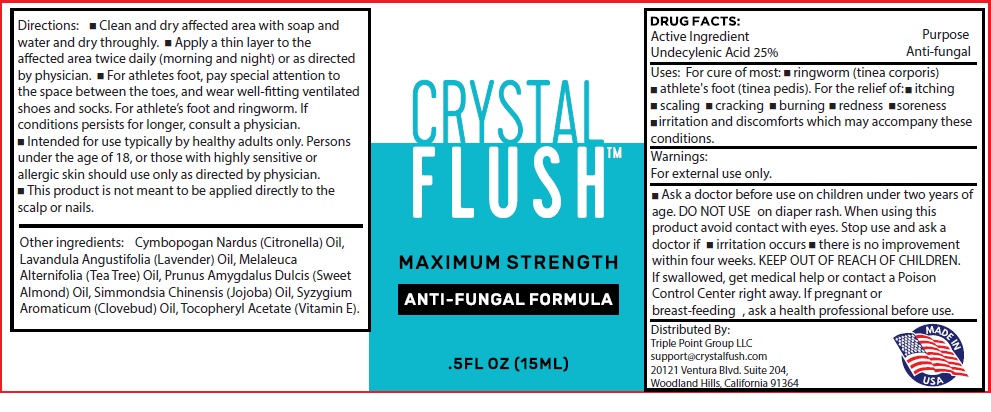 DRUG LABEL: FLUSH Maximum Strength Antifungal formula
NDC: 80569-084 | Form: LIQUID
Manufacturer: Triple Point Group, LLC
Category: otc | Type: HUMAN OTC DRUG LABEL
Date: 20231111

ACTIVE INGREDIENTS: UNDECYLENIC ACID 250 mg/1 mL
INACTIVE INGREDIENTS: CITRONELLA OIL; LAVENDER OIL; TEA TREE OIL; ALMOND OIL; JOJOBA OIL; CLOVE OIL; .ALPHA.-TOCOPHEROL ACETATE

CRYSTAL FLUSH Maximum Strength Antifungal formula

Active Ingredient

Undecylenic Acid 25%

Purpose

Anti-fungal

Uses:

For cure of most: • ringworm (tinea corporis) • athlete's foot (tinea pedis). For the relief of: • itching• scaling • cracking • burning • redness • soreness • irritation and discomforts which may accompany these conditions.

Warnings:

For external use only.

Ask a doctor before use

on children under two years of age

DO NOT USE

on diaper rash.

When using this product

avoid contact with eyes.

Stop use and ask a doctor if

- irritation occurs
- there is no improvement within four weeks.

KEEP OUT OF REACH OF CHILDREN.

If swallowed, get medical help or contact a Poison Control Center right away.

If pregnant or breast-feeding,

ask a health professional before use.

Directions:

- Clean and dry affected area with soap and water and dry throughly.
- Apply a thin layer to the affected area twice daily (morning and night) or as directed by physician.
- For athletes foot, pay special attention to the space between the toes, and wear well-fitting ventilated shoes and socks. For athlete's foot and ringworm. If Conditions persists for longer, consult a physician.
- Intended for use typically by healthy adults only. Persons under the age of 18, or those with highly sensitive or allergic skin should use only as directed by physician.
- This product is not meant to be applied directly to the Scalp or nails.

Other ingredients:

Cymbopogan Nardus (Citronella) Oil, Lavandula Angustifolia (Lavender) Oil, Melaleuca Alternifolia (Tea Tree) Oil, Prunus Amygdalus Dulcis (Sweet Almond) Oil, Simmondsia Chinensis (Jojoba) Oil, Syzygium Aromaticum (Clovebud) Oil, Tocopheryl Acetate (Vitamin E).